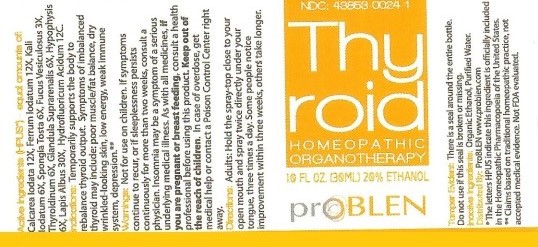 DRUG LABEL: Thyroid
NDC: 43853-0024 | Form: SPRAY
Manufacturer: ProBlen
Category: homeopathic | Type: HUMAN OTC DRUG LABEL
Date: 20200928

ACTIVE INGREDIENTS: FERROUS IODIDE 12 [hp_X]/30 mL; POTASSIUM IODIDE 6 [hp_X]/30 mL; SPONGIA OFFICINALIS SKELETON, ROASTED 6 [hp_X]/30 mL; FUCUS VESICULOSUS 3 [hp_X]/30 mL; THYROID, UNSPECIFIED 6 [hp_X]/30 mL; SUS SCROFA ADRENAL GLAND 6 [hp_X]/30 mL; SUS SCROFA PITUITARY GLAND 6 [hp_X]/30 mL; CALCIUM HEXAFLUOROSILICATE 30 [hp_X]/30 mL; HYDROFLUORIC ACID 12 [hp_C]/30 mL; CALCIUM IODIDE 12 [hp_X]/30 mL
INACTIVE INGREDIENTS: ALCOHOL; WATER

Thyroid

Active Ingredients (HPUS*) equal amounts of:

Calcarea Iodata 12X, Ferrum Iodatum 12X, Kali Iodatum 6X, Spongia Tosta 6X, Fucus Vesiculosus 3X, Thyroidinum 6X, Glandula Suprarenalis 6X, Hypophysis 6X, Lapis Albus 30X, Hydrofluoricum Acidum 12C.

* The letters HPUS indicate this indredient is officially included in the Homeopathic Pharmacopoeia of the United States.

** Claims based on traditional homeopathic practices, not accepted medical evidence. Not FDA evaluated.

INDICATIONS AND USAGE

Indications: Temporarily supports the body to rebalance thyroid output. Symptoms of imbalanced thyroid output. Symptoms of imbalanced thyroid may include: poor muscle/fat balance, dry wrinkled-looking skin, low energy, weak immune system, depression.**

WARNINGS

Warnings: Not for use on children. If symptoms continue to recur, or if sleeplessness persists continously for more than two weeks, consult a physician. Insomnia may be a symptom of a serious underlying medical illness. As with all medicines, if you are pregnant or breast feeding, consult a health professional before using this product. Keep out of reach of children. In case of overdose, get medical help or contact a Poison Control Center right away.

Keep out of reach of children.

DOSAGE AND ADMINISTRATION

Directions: Adults: Hold the spray-top close to your open mouth and spray twice directly under your tongue, three times a day. Some people notice improvements within three weeks, others take longer.

OTHER SAFETY INFORMATION

Tamper Evident: There is a seal around the entire bottle. Do not use if this seal is broken or missing.

Inactive ingredients: Organic Ethanol, Purified Water.

QUESTIONS

Distributed By: ProBLEN www.problen.com

PACKAGE LABEL

NDC: 43853-0024-1

Thy

roid

HOMEOPATHIC

ORGANOTHERAPY

1.0 FL OZ 20% ETHANOL

prOBLEN

PURPOSE

Temporarily supports the body to rebalance thyroid output. Symptoms of imbalanced thyroid output. Symptoms of imbalanced thyroid may include: poor muscle/fat balance, dry wrinkled-looking skin, low energy, weak immune system, depression.**